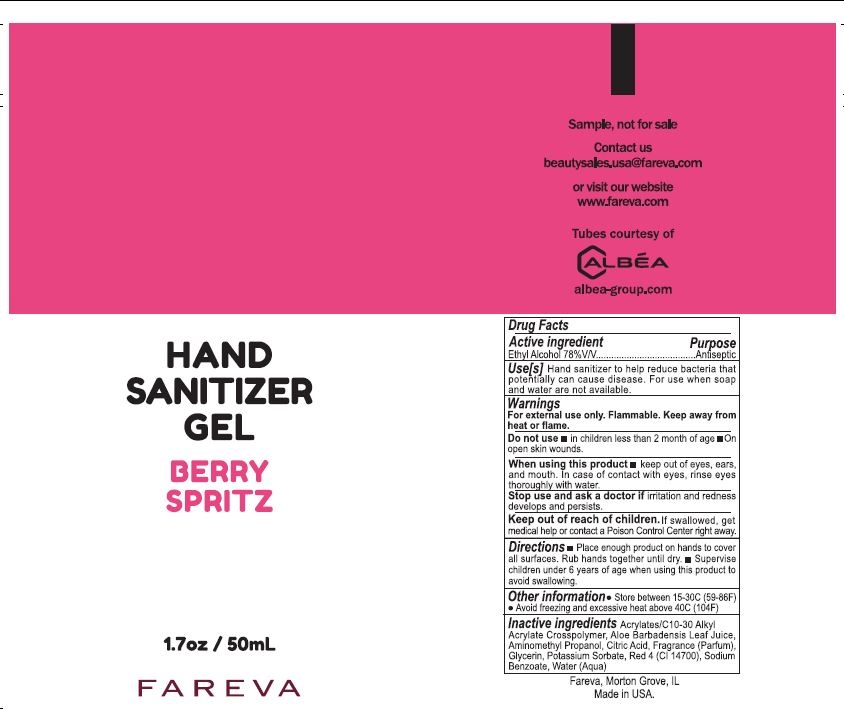 DRUG LABEL: Hand Sanitizer
NDC: 72686-188 | Form: GEL
Manufacturer: Fareva Morton Grove, Inc.
Category: otc | Type: HUMAN OTC DRUG LABEL
Date: 20201215

ACTIVE INGREDIENTS: ALCOHOL 78 mL/100 mL
INACTIVE INGREDIENTS: AMINOMETHYLPROPANOL; GLYCERIN; FRAGRANCE JUNIPERBERRY ORANGE ORC2000843; WATER; CARBOMER INTERPOLYMER TYPE A (55000 CPS); POTASSIUM SORBATE; SODIUM BENZOATE; CITRIC ACID MONOHYDRATE; ALOE; FD&C RED NO. 4

a. Alcohol (ethanol) (USP or Food Chemical Codex (FCC) grade) (77%, volume/volume (v/v)) in an aqueous solution denatured according to Alcohol and Tobacco Tax and Trade Bureau regulations in 27 CFR part 20.
b. Glycerin

c. FRAGRANCE (PARFUM)
d. ACRYLATES/C10-30 ALKYL ACRYLATE CROSSPOLYMER
e. ALOE BARBADENSIS LEAF JUICE

f. AMINOMETHYL PROPANOL

g. RED 4 (CI 14700)

h. CITRIC ACID

i. SODIUM BENZOATE

j. POTASSIUM SORBATE

Active Ingredient(s)

Alcohol 78% v/v. Purpose: Antiseptic

Purpose

Antiseptic

Use

Hand Sanitizer to help reduce bacteria that potentially can cause disease. For use when soap and water are not available.

Warnings

For external use only. Flammable. Keep away from heat or flame

Do not use

- in children less than 2 months of age
- on open skin wounds

When using this product keep out of eyes, ears, and mouth. In case of contact with eyes, rinse eyes thoroughly with water.

Stop use and ask a doctor if irritation and redness develops and persists.

Keep out of reach of children. If swallowed, get medical help or contact a Poison Control Center right away.

Directions

- Place enough product on hands to cover all surfaces. Rub hands together until dry.
- Supervise children under 6 years of age when using this product to avoid swallowing.

Other information

- Store between 15-30C (59-86F)
- Avoid freezing and excessive heat above 40C (104F)

Inactive ingredients

Acrylates/C10-30 Acrylate Crosspolymer, Aloe Barbadensis Leaf Juice, Aminomethyl Propanol, Citric Acid, Fragrance, Glycerin, Potassium Sorbate, Red 4 (CI 14700), Sodium Benzoate, Water

Package Label - Principal Display Panel

50 mL NDC: 72686-188-05